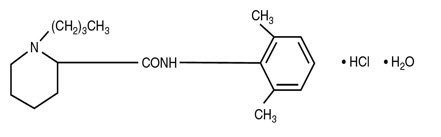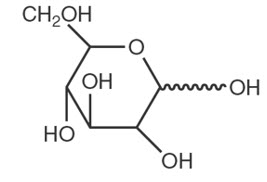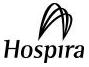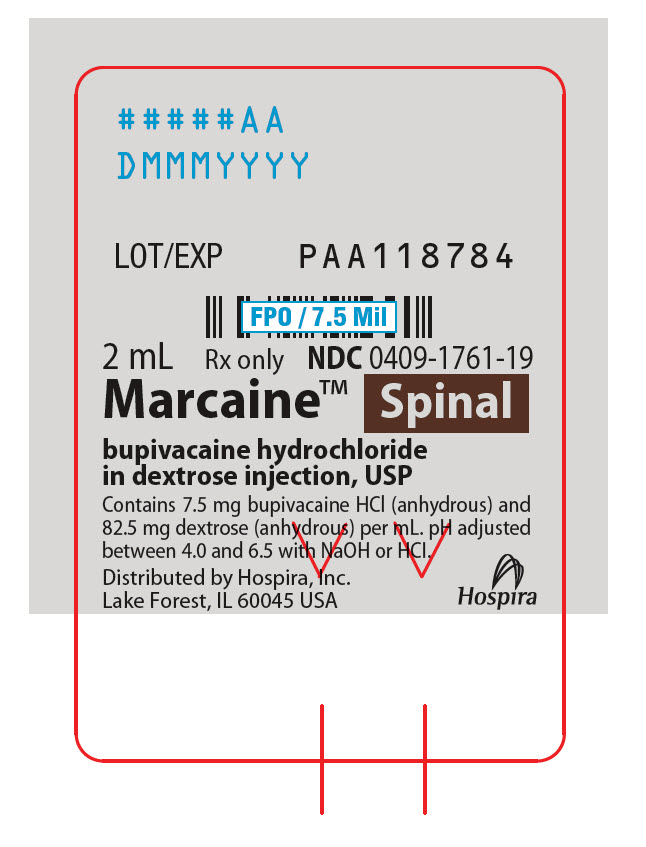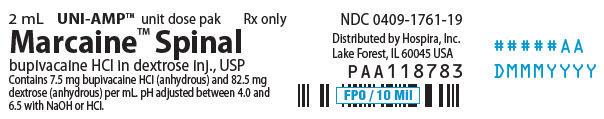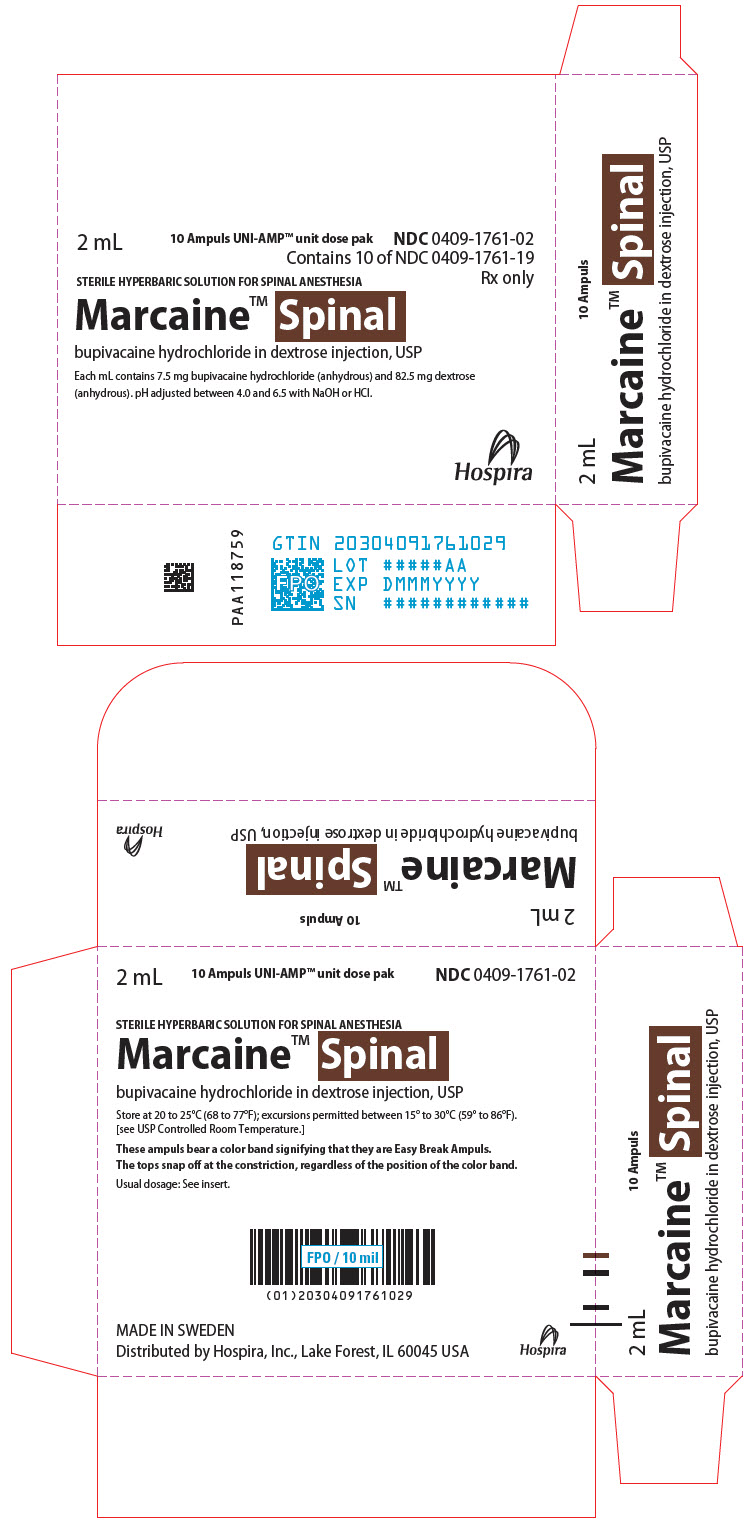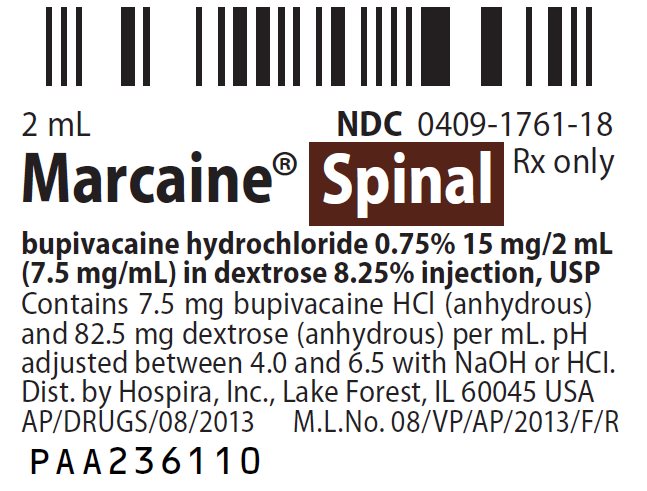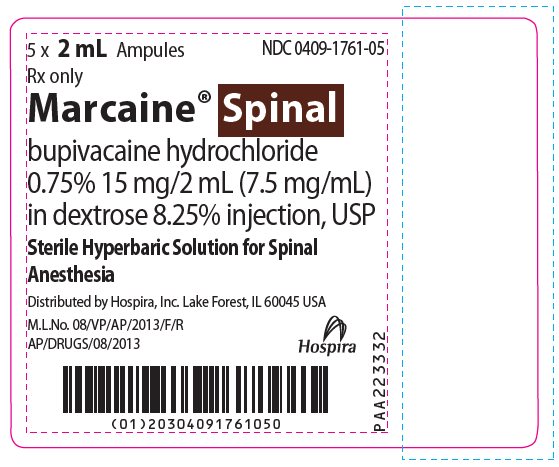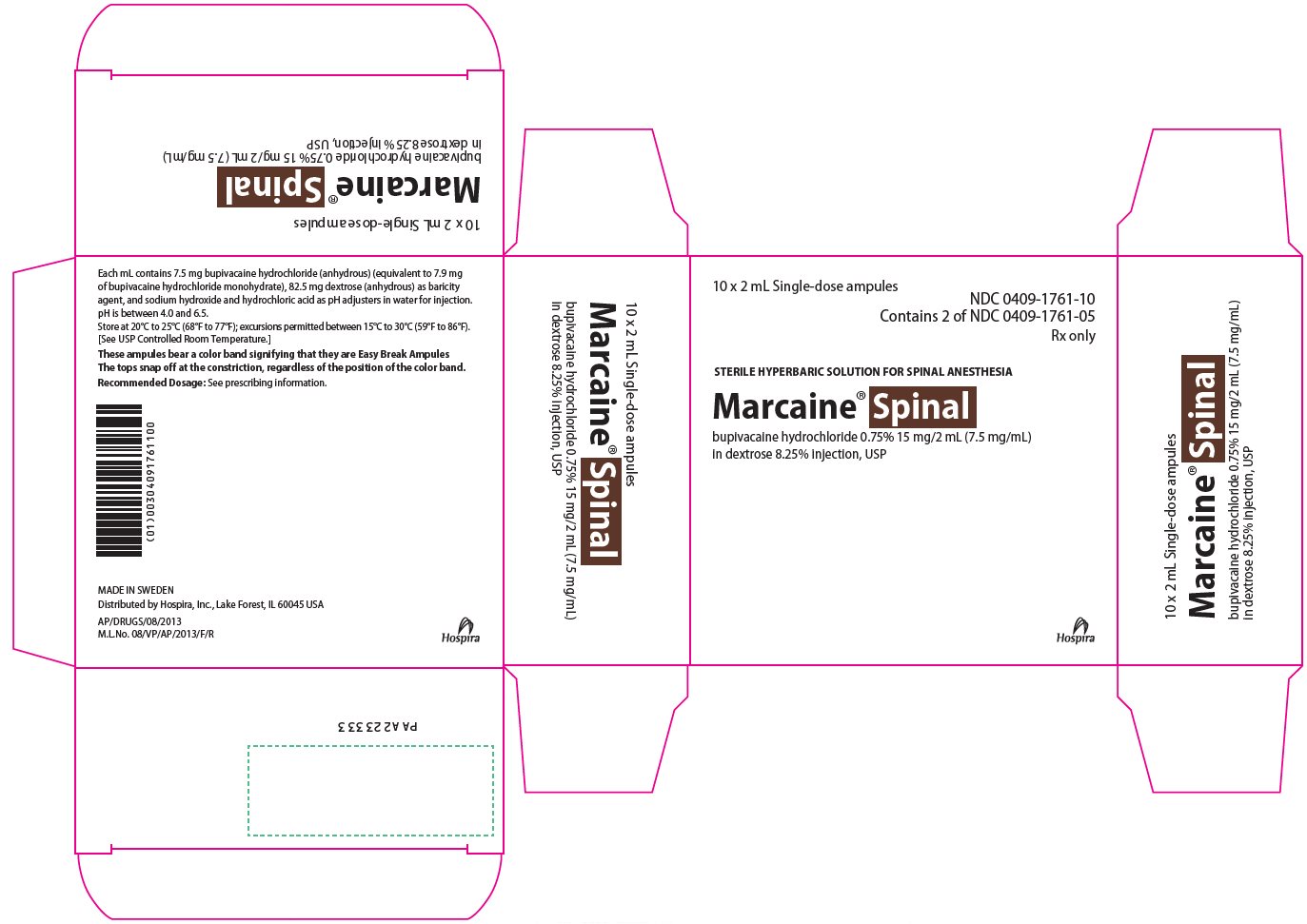 DRUG LABEL: Marcaine Spinal
NDC: 0409-1761 | Form: INJECTION, SOLUTION
Manufacturer: Hospira, Inc.
Category: prescription | Type: HUMAN PRESCRIPTION DRUG LABEL
Date: 20250513

ACTIVE INGREDIENTS: BUPIVACAINE HYDROCHLORIDE 7.5 mg/1 mL
INACTIVE INGREDIENTS: ANHYDROUS DEXTROSE 82.5 mg/1 mL; SODIUM HYDROXIDE; HYDROCHLORIC ACID; WATER

HIGHLIGHTS OF PRESCRIBING INFORMATION

These highlights do not include all the information needed to use MARCAINE® SPINAL safely and effectively. See full prescribing information for MARCAINE® SPINAL.
MARCAINE® SPINAL (bupivacaine hydrochloride in dextrose injection) for subarachnoid injection
Initial U.S. Approval: 1984

1 INDICATIONS AND USAGE

MARCAINE SPINAL is an amide-local anesthetic indicated in adults for subarachnoid injection for the production of subarachnoid block (spinal anesthesia). (1)

2 DOSAGE AND ADMINISTRATION

The dosage of MARCAINE SPINAL administered varies with the anesthetic procedure, the vascularity of the tissues, the number of neuronal segments to be blocked, the depth of anesthesia and degree of muscle relaxation required, the duration of anesthesia desired, individual tolerance, and the physical condition of the patient. Administer the smallest dosage and concentration required to produce the desired result. The following are general dosage guidelines:

- MARCAINE SPINAL 6 mg is generally adequate for vaginal delivery. (2.2)
- MARCAINE SPINAL 7.5 mg is generally adequate for spinal anesthesia for lower extremity and perineal procedures. (2.2)
- MARCAINE SPINAL 12 mg is generally adequate for lower abdominal procedures. (2.2)
- MARCAINE SPINAL 7.5 mg to 10.5 mg is generally adequate for Cesarean section. (2.2)

3 DOSAGE FORMS AND STRENGTHS

Injection: 15 mg/2 mL (7.5 mg/mL) in single-dose glass ampules. (3)

4 CONTRAINDICATIONS

- Intravenous regional anesthesia (Bier Block). (4)
- Septicemia. (4)
- Severe hemorrhage, severe hypotension or shock, and arrhythmias, such as complete heartblock, which severely reduce cardiac output. (4)
- Known hypersensitivity to bupivacaine or to any local anesthetic agent of the amide-type or to other components of MARCAINE SPINAL. (4)
- Local infection at the site of proposed lumbar puncture. (4)

5 WARNINGS AND PRECAUTIONS

- Use of Spinal Anesthetics During Uterine Contractions: Spinal anesthetics, including MARCAINE SPINAL, should not be injected during uterine contractions because cerebrospinal fluid current may carry the drug further cephalad than desired, resulting in a high motor block. (5.1)
- Patients with Hypertension: Sympathetic blockade due to spinal anesthesia may result in peripheral vasodilation and hypotension. Monitor blood pressure frequently. Hypotension may be controlled by administration of vasoconstrictor agents in titrated dosages depending on the severity of hypotension and response to treatment. Monitor the onset of adequate spinal anesthesia frequently. (5.2)
- Dose-Related Toxicity: Monitor cardiovascular and respiratory vital signs and patient's state of consciousness after injection of MARCAINE SPINAL. (5.3)
- Risk of Systemic Toxicities with Unintended Intravascular Injection: Unintended intravascular injection may be associated with systemic toxicities, including CNS or cardiorespiratory depression and coma, progressing ultimately to respiratory arrest. Aspirate for blood and cerebrospinal fluid (where applicable) prior to each dose. (5.4)
- Methemoglobinemia: Cases of methemoglobinemia have been reported in association with local anesthetic use. See full prescribing information for more detail on managing these risks. (5.5)
- Risk of Cardiac Arrest with Use of Epidural Bupivacaine in Obstetrical Anesthesia: There have been reports of cardiac arrest during use of MARCAINE 0.75% solution for epidural anesthesia in obstetrical patients. MARCAINE SPINAL (bupivacaine hydrochloride in dextrose injection) is recommended for spinal anesthesia in obstetrical patients. (5.6)
- Chondrolysis with Intra-Articular Infusion: Intra-articular infusions of local anesthetics including bupivacaine following arthroscopic and other surgical procedures is an unapproved use, and there have been post-marketing reports of chondrolysis in patients receiving such infusions. (5.7)
- Risk of Cardiac Arrest with Intravenous Regional Anesthesia Use (Bier Block): There have been reports of cardiac arrest and death during the use of bupivacaine for intravenous regional anesthesia (Bier Block). (5.8)

6 ADVERSE REACTIONS

Most common adverse reactions are hypotension due to loss of sympathetic tone, and diaphragmatic paralysis or hypoventilation due to cephalad spread and high motor block. (6)

To report SUSPECTED ADVERSE REACTIONS, contact Pfizer Inc. at 1-800-438-1985 or FDA at 1-800-FDA-1088 or www.fda.gov/medwatch.

7 DRUG INTERACTIONS

- Local Anesthetics: The toxic effects of local anesthetics are additive. Monitor for neurologic and cardiovascular effects when additional local anesthetics are administered. (7.1)
- Drugs Associated with Methemoglobinemia: Patients are at increased risk of developing methemoglobinemia when concurrently exposed to nitrates, nitrites, local anesthetics, antineoplastic agents, antibiotics, antimalarials, anticonvulsants, and other drugs. (7.2)

8 USE IN SPECIFIC POPULATIONS

- Pediatric Use: Administration of MARCAINE SPINAL in patients younger than 18 years is not recommended. (8.4)
- Geriatric Use: Patients 65 years and over, particularly those with hypertension, may be at increased risk for developing hypotension while undergoing spinal anesthesia with MARCAINE SPINAL. (8.5)
- Moderate to Severe Hepatic Impairment: Consider increased monitoring for bupivacaine systemic toxicity. (8.6)

FULL PRESCRIBING INFORMATION

1 INDICATIONS AND USAGE

MARCAINE SPINAL is indicated for subarachnoid injection in adults for the production of subarachnoid block (spinal anesthesia).

2 DOSAGE AND ADMINISTRATION

2.1 Important Dosage and Administration Information

- Visually inspect this product for particulate matter and discoloration prior to administration. MARCAINE SPINAL is a clear, colorless solution. Do not administer solutions which are discolored or contain particulate matter.
- Mixing or the prior or intercurrent use of any other local anesthetic with MARCAINE SPINAL is not recommended because of insufficient data on the clinical use of such mixtures.
- Discard unused portions of MARCAINE SPINAL following initial use.

Administration Precautions

- MARCAINE SPINAL is to be administered in carefully adjusted dosages by or under the supervision of experienced clinicians who are well versed in the diagnosis and management of dose-related toxicity and other acute emergencies which might arise from the block to be employed.
- Use MARCAINE SPINAL only if the following are immediately available: oxygen, cardiopulmonary resuscitative equipment and drugs, and the personnel resources needed for proper management of toxic reactions and related emergencies [see Warnings and Precautions (5.3), Adverse Reactions (6), Overdosage (10)].
- The toxic effects of local anesthetics are additive. Monitor for neurologic and cardiovascular effects related to local anesthetic systemic toxicity when additional local anesthetics are administered with MARCAINE SPINAL [see Warnings and Precautions (5.3), Drug Interactions (7.1), Overdosage (10)].
- Aspirate for blood and cerebrospinal fluid prior to injecting MARCAINE SPINAL, for both the initial dose and all subsequent doses (where applicable), to avoid intravascular injection and to confirm entry into the subarachnoid space. Aspiration of cerebrospinal fluid into a MARCAINE SPINAL-filled syringe will result in an identifiable swirl in the solution. A negative aspiration for blood does not ensure against an intravascular injection [see Warnings and Precautions (5.4)].
- Avoid rapid injection of MARCAINE SPINAL.
- The patient should have an indwelling intravenous catheter to assure adequate intravenous access. The lowest dosage of MARCAINE SPINAL that results in effective spinal anesthesia should be used to avoid a high motor block and serious adverse reactions.
- Perform careful and constant monitoring of cardiovascular and respiratory (adequacy of oxygenation and ventilation) vital signs and the patient's level of consciousness during spinal anesthesia.

Conditions Which May Preclude Use of Spinal Anesthesia

The following conditions may preclude the use of spinal anesthesia, depending upon the physician's evaluation of the patient:

- Pre-existing diseases of the central nervous system (CNS), such as those attributable to pernicious anemia, poliomyelitis, syphilis, or tumor.
- Hematological disorders predisposing to coagulopathies or patients on anticoagulant therapy. Trauma to a blood vessel during the conduct of spinal anesthesia may, in some instances, result in uncontrollable CNS hemorrhage, soft tissue hemorrhage, or development of a hematoma.
- Chronic backache and preoperative headache.
- Hypotension and hypertension.
- Technical problems (persistent paresthesias, persistent bloody tap).
- Arthritis or spinal deformity.
- Extremes of age.
- Psychosis, dementia, or other illnesses resulting in poor patient cooperation.

2.2 Recommended Dosages of MARCAINE SPINAL

The dosage of MARCAINE SPINAL administered varies with the anesthetic procedure, the vascularity of the tissues, the number of neuronal segments to be blocked, the depth of anesthesia and degree of muscle relaxation required, the duration of anesthesia desired, individual tolerance, and the physical condition of the patient. Administer the smallest dosage and concentration required to produce the desired result.

The extent and degree of spinal anesthesia depend upon several factors including dosage, baricity of the anesthetic solution, volume of solution, force of injection, level of puncture, and position of the patient during and immediately after injection.

In recommended doses, MARCAINE SPINAL produces complete motor and sensory block.

The following table summarizes general dosage guidelines for adult patients for the procedures described:

PROCEDURES | DOSAGE GUIDELINES
Vaginal Delivery | Starting dose, 6 mg (0.8 mL)
Lower Extremity and Perineal Procedures, such as:; - transurethral resection of the prostate (TURP) - vaginal hysterectomy | 7.5 mg (1 mL)
Lower Abdominal Procedures, such as:; - abdominal hysterectomy - tubal ligation - appendectomy | 12 mg (1.6 mL)
Cesarean Section | 7.5 mg to 10.5 mg (1 mL to 1.4 mL)

3 DOSAGE FORMS AND STRENGTHS

MARCAINE SPINAL (bupivacaine hydrochloride in dextrose injection) is a clear, colorless solution available as:

- 15 mg/2 mL (7.5 mg/mL) in single-dose glass ampules.

4 CONTRAINDICATIONS

MARCAINE SPINAL is contraindicated in:

- intravenous regional anesthesia (Bier Block) [see Warnings and Precautions (5.8)].
- patients with septicemia.
- patients with severe hemorrhage, severe hypotension or shock, due to a reduced cardiac output.
- patients with clinically significant arrhythmias, such as complete heartblock, due a reduced cardiac output.
- patients with a known hypersensitivity to bupivacaine or to any local anesthetic agent of the amide-type or to other components of MARCAINE SPINAL.
  - patients with local infection at the site of proposed lumbar puncture.

5 WARNINGS AND PRECAUTIONS

5.1 Use of Spinal Anesthetics During Uterine Contractions

Spinal anesthetics including MARCAINE SPINAL should not be injected during uterine contractions because cerebrospinal fluid current may carry the drug further cephalad than desired, resulting in a high motor block.

5.2 Patients with Hypertension

Sympathetic blockade due to spinal anesthesia may result in peripheral vasodilation and hypotension, the extent of which depends on the number of dermatomes blocked. Patients over 65 years, particularly those with hypertension, may be at increased risk for experiencing the hypotensive effects of MARCAINE SPINAL. Monitor blood pressure frequently, especially in the early phases of anesthesia. Hypotension may be controlled by administration of vasoconstrictor agents in titrated dosages depending on the severity of hypotension and response to treatment. Monitor the onset of adequate spinal anesthesia because it is not always possible to control the level of anesthesia after subarachnoid injection of MARCAINE SPINAL.

5.3 Dose-Related Toxicity

The safety and effectiveness of MARCAINE SPINAL depend on proper dosage, correct technique, adequate precautions, and readiness for emergencies. Careful and constant monitoring of cardiovascular and respiratory (adequacy of oxygenation and ventilation) vital signs and the patient's state of consciousness should be performed after injection of MARCAINE SPINAL solutions.

Possible early warning signs of central nervous system (CNS) toxicity are restlessness, anxiety, incoherent speech, lightheadedness, numbness and tingling of the mouth and lips, metallic taste, tinnitus, dizziness, blurred vision, tremors, twitching, CNS depression, or drowsiness. Delay in proper management of dose-related toxicity, hypoventilation from any cause, and/or altered sensitivity may lead to the development of acidosis, cardiac arrest, and possibly death.

The patient should have an indwelling intravenous catheter to assure adequate intravenous access. Use the lowest dosage of MARCAINE SPINAL that results in effective anesthesia to avoid serious adverse reactions. Avoid rapid injection of a large volume of MARCAINE SPINAL.

Injection of repeated doses of MARCAINE SPINAL may cause significant increases in plasma bupivacaine levels with each repeated dose due to slow accumulation of the drug or its metabolites, or to slow metabolic degradation. Tolerance to elevated blood levels varies with the status of the patient. Debilitated, elderly patients and acutely ill patients should be given reduced doses commensurate with their age and physical status. Reduced doses may be indicated in patients with increased intra-abdominal pressure (including obstetrical patients), if otherwise suitable for spinal anesthesia.

5.4 Risk of Systemic Toxicities with Unintended Intravascular Injection

Unintended intravascular injection of MARCAINE SPINAL may be associated with systemic toxicities, including CNS or cardiorespiratory depression and coma, progressing ultimately to respiratory arrest [see Adverse Reactions (6)].

Aspirate for blood and cerebrospinal fluid before injecting MARCAINE SPINAL, for both the initial dose and all subsequent doses (where applicable), to confirm entry into the subarachnoid space and to avoid intravascular injection. Aspiration of cerebrospinal fluid into a MARCAINE SPINAL-filled syringe will result in an identifiable swirl in the solution. A negative aspiration for blood does not ensure against an intravascular injection.

5.5 Methemoglobinemia

Cases of methemoglobinemia have been reported in association with local anesthetic use. Although all patients are at risk for methemoglobinemia, patients with glucose 6 phosphate dehydrogenase deficiency, congenital or idiopathic methemoglobinemia, cardiac or pulmonary compromise, infants under 6 months of age, and concurrent exposure to oxidizing agents or their metabolites are more susceptible to developing clinical manifestations of the condition [see Drug Interactions (7.2)]. If local anesthetics must be used in these patients, close monitoring for symptoms and signs of methemoglobinemia is recommended.

Signs of methemoglobinemia may occur immediately or may be delayed some hours after exposure, and are characterized by a cyanotic skin discoloration and/or abnormal coloration of the blood. Methemoglobin levels may continue to rise; therefore, immediate treatment is required to avert more serious CNS and cardiovascular adverse effects, including seizures, coma, arrhythmias, and death. Discontinue MARCAINE SPINAL and any other oxidizing agents. Depending on the severity of the signs and symptoms, patients may respond to supportive care, i.e., oxygen therapy, hydration. A more severe clinical presentation may require treatment with methylene blue, exchange transfusion, or hyperbaric oxygen.

5.6 Risk of Cardiac Arrest with Use of Epidural Bupivacaine in Obstetrical Anesthesia

There have been reports of cardiac arrest with difficult resuscitation or death during use of MARCAINE for epidural anesthesia in obstetrical patients. In most cases, this has followed use of MARCAINE 0.75%, not MARCAINE SPINAL. The package insert for MARCAINE hydrochloride for epidural, nerve block, etc., has a more complete discussion of preparation for, and management of cardiac arrest following epidural administration. MARCAINE SPINAL (bupivacaine hydrochloride in dextrose injection) is recommended for spinal anesthesia in obstetrical patients.

5.7 Chondrolysis with Intra-Articular Infusion

Intra-articular infusions of local anesthetics including bupivacaine following arthroscopic and other surgical procedures is an unapproved use, and there have been post-marketing reports of chondrolysis in patients receiving such infusions. The majority of reported cases of chondrolysis have involved the shoulder joint; cases of gleno-humeral chondrolysis have been described in pediatric and adult patients following intra-articular infusions of local anesthetics with and without epinephrine for periods of 48 to 72 hours. There is insufficient information to determine whether shorter infusion periods are not associated with chondrolysis. The time of onset of symptoms, such as joint pain, stiffness, and loss of motion can be variable, but may begin as early as the 2nd month after surgery. Currently, there is no effective treatment for chondrolysis; patients who experienced chondrolysis have required additional diagnostic and therapeutic procedures and some required arthroplasty or shoulder replacement.

5.8 Risk of Cardiac Arrest with Intravenous Regional Anesthesia Use (Bier Block)

There have been reports of cardiac arrest and death during the use of bupivacaine for intravenous regional anesthesia (Bier Block). Information on safe dosages and techniques of administration of MARCAINE SPINAL in this procedure is lacking. Therefore, MARCAINE SPINAL is contraindicated for use with this technique [see Contraindications (4)].

5.9 Patients with Severe Disturbances of Cardiac Rhythm, Shock, or Heart Block

Consider alternate anesthetic techniques in patients with severe disturbances of cardiac rhythm, shock, or heart block [see Contraindications (4)].

5.10 Risk of Toxicity in Patients with Hepatic Impairment

Because amide-type local anesthetics such as bupivacaine are metabolized by the liver, consider reduced dosing and increased monitoring for bupivacaine systemic toxicity in patients with moderate to severe hepatic impairment who are treated with MARCAINE SPINAL [see Use in Specific Populations (8.6)]. Most information regarding dose-related hepatic impairment is based on larger dosages of bupivacaine administered for other neuraxial, peripheral nerve, or fascial plane blocks.

5.11 Risk of Use in Patients with Impaired Cardiovascular Function

MARCAINE SPINAL should be given in reduced doses in patients with impaired cardiovascular function (e.g., hypotension, heartblock, valvular abnormalities) because they may be less able to compensate for functional changes associated with the sympathetic blockade observed after subarachnoid administration of MARCAINE SPINAL and the prolongation of AV conduction produced by the drug. Monitor patients closely for blood pressure, heart rate, and ECG changes.

6 ADVERSE REACTIONS

The following clinically significant adverse reactions have been reported and described in other sections of the labeling:

- Allergic-Type Reactions [see Contraindications (4)]
- Dose-Related Toxicity [see Warnings and Precautions (5.3)]
- Systemic Toxicities with Unintended Intravascular Injection [see Warnings and Precautions (5.4)]
- Methemoglobinemia [see Warnings and Precautions (5.5)]
- Cardiac Arrest in Obstetrical Anesthesia [see Warnings and Precautions (5.6)]
- Chondrolysis with Intra-Articular Infusion [see Warnings and Precautions (5.7)]
- Cardiac Arrest with Intravenous Regional Anesthesia Use [see Contraindications (4), Warnings and Precautions (5.8)]

The following adverse reactions from voluntary reports or clinical studies have been reported with bupivacaine. Because many of these reactions were reported voluntarily from a population of uncertain size, it is not always possible to reliably estimate their frequency or establish a causal relationship to drug exposure.

Adverse reactions to MARCAINE SPINAL are characteristic of those associated with other amide-type local anesthetics. A major cause of adverse reactions to MARCAINE SPINAL is due to cephalad extension of the motor level of anesthesia and/or excessive plasma levels, which may be due to overdosage, unintentional intravascular injection, or slow metabolic degradation.

The most commonly encountered acute adverse reactions that demand immediate counter-measures following the administration of spinal anesthesia were hypotension due to loss of sympathetic tone and respiratory paralysis or underventilation due to cephalad extension of the motor level of anesthesia. These have led to cardiac arrest if untreated. In addition, dose-related convulsions and cardiovascular collapse have resulted from diminished tolerance, rapid absorption from the injection site, or from unintentional intravascular injection of a local anesthetic solution.

Respiratory System: Respiratory paralysis or underventilation have been noted as a result of cephalad spread of spinal anesthesia and has led to secondary hypoxic cardiac arrest when untreated. Preanesthetic medication, intraoperative anesthetics, analgesics, and sedatives, as well as surgical manipulation, may contribute to underventilation. This has usually been noted within minutes of the injection of spinal anesthetic solution, but because of differing maximal onset times, differing intercurrent drug usage, and differing surgical manipulation, it may occur at any time during surgery or the immediate recovery period.

Cardiac Disorders: Hypotension due to loss of sympathetic tone has been commonly encountered following spinal anesthesia. This has been more commonly observed in elderly patients, particularly those with hypertension, and patients with reduced blood volume, reduced interstitial fluid volume, cephalad spread of the local anesthetic, and/or mechanical obstruction of venous return. Nausea and vomiting have been frequently associated with hypotensive episodes following the administration of spinal anesthesia. High doses, or inadvertent intravascular injection, have led to high plasma levels and related depression of the myocardium, decreased cardiac output, bradycardia, heart block, ventricular arrhythmias, and cardiac arrest [see Warnings and Precautions (5.4)].

Nervous System Disorders: Respiratory paralysis or underventilation secondary to cephalad spread of the level of spinal anesthesia (see Respiratory System) and hypotension for the same reason (see Cardiac Disorders) have been the two most commonly encountered CNS-related adverse observations which demand immediate counter-measures.

High doses or inadvertent intravascular injection have led to high plasma levels and related CNS toxicity. Adverse reactions were characterized by excitation and/or depression of the CNS and included restlessness, anxiety, dizziness, tinnitus, blurred vision, tremors, convulsions, drowsiness, unconsciousness, and respiratory arrest.

The incidences of adverse neurologic reactions associated with the use of local anesthetics may be related to the total dose of local anesthetic administered and are also dependent upon the particular drug used, the route of administration, and the physical status of the patient.

Convulsions: Incidence varied with the procedure used and the total dose administered. In a survey of studies of epidural anesthesia, overt toxicity progressing to convulsions occurred in approximately 0.1% of local anesthetic administrations. The incidences of adverse neurologic reactions associated with the use of local anesthetics may be related to the total dose of local anesthetic administered and are also dependent upon the particular drug used, the route of administration, and the physical status of the patient.

Neurologic effects following spinal anesthesia have included loss of perineal sensation and sexual function; persistent anesthesia, paresthesia, weakness and paralysis of the lower extremities, and loss of sphincter control with slow, incomplete, or no recovery; hypotension, high or total spinal block; urinary retention; headache; backache; septic meningitis, meningismus; arachnoiditis; slowing of labor; increased incidence of forceps delivery; shivering; cranial nerve palsies due to traction on nerves from loss of cerebrospinal fluid; and fecal and urinary incontinence.

Immune System Disorders: Allergic-type reactions have occurred as a result of sensitivity to bupivacaine. These reactions were characterized by signs such as urticaria, pruritus, erythema, angioneurotic edema (including laryngeal edema), tachycardia, sneezing, nausea, vomiting, dizziness, syncope, excessive sweating, elevated temperature, and severe hypotension. Cross sensitivity among members of the amide-type local anesthetic group has been reported.

7 DRUG INTERACTIONS

7.1 Local Anesthetics

The toxic effects of local anesthetics are additive. If coadministration of other local anesthetics with MARCAINE SPINAL cannot be avoided, monitor patients for neurologic and cardiovascular effects related to local anesthetic systemic toxicity [see Dosage and Administration (2.1), Warnings and Precautions (5.3)].

7.2 Drugs Associated with Methemoglobinemia

Patients who are administered MARCAINE SPINAL are at increased risk of developing methemoglobinemia when concurrently exposed to the following drugs, which could include other local anesthetics [see Warnings and Precautions (5.5)].

Examples of Drugs Associated with Methemoglobinemia:

Class | Examples
Nitrates/Nitrites | nitric oxide, nitroglycerin, nitroprusside, nitrous oxide
Local anesthetics | articaine, benzocaine, bupivacaine, lidocaine, mepivacaine, prilocaine, procaine, ropivacaine, tetracaine
Antineoplastic agents | cyclophosphamide, flutamide, hydroxyurea, isofamide, rasburicase
Antibiotics | dapsone, nitrofurantoin, para-aminosalicylic acid, sulfonamides
Antimalarials | chloroquine, primaquine
Anticonvulsants | phenobarbital, phenytoin, sodium valproate
Other drugs | acetaminophen, metoclopramide, quinine, sulfasalazine

8 USE IN SPECIFIC POPULATIONS

8.1 Pregnancy

Risk Summary

The available data on the use of MARCAINE SPINAL in pregnant women do not establish the presence or absence of developmental toxicity related to the use of MARCAINE SPINAL.

In animal studies, embryo-fetal lethality was noted when bupivacaine was administered subcutaneously to pregnant rabbits during organogenesis and decreased pup survival was observed in a rat pre- and post-natal developmental study (dosing from implantation through weaning). These effects were observed at dose levels approximately 30 times the daily maximum recommended human dose (MRHD) on a body surface area (BSA) basis. Based on animal data, advise pregnant women of the potential risk to a fetus (see Data).

Local anesthetics rapidly cross the placenta, and when used for epidural, caudal, or pudendal block anesthesia, can cause varying degrees of maternal, fetal, and neonatal toxicity [see Clinical Pharmacology (12.3)]. The incidence and degree of toxicity depend upon the procedure performed, the type, and amount of drug used, and the technique of drug administration. Adverse reactions in the parturient, fetus, and neonate involve alterations of the CNS, peripheral vascular tone, and cardiac function.

If this drug is used during pregnancy or if the patient becomes pregnant while taking this drug, inform the patient of the potential hazard to the fetus. The estimated background risk of major birth defects and miscarriage for the indicated populations are unknown. In the U.S. general population, the estimated background risk of major birth defects and miscarriage in clinically recognized pregnancies is 2–4% and 15–20%, respectively.

Clinical Considerations

Maternal Adverse Reactions

Maternal hypotension has resulted from regional and neuraxial anesthesia. Local anesthetics produce vasodilation by blocking sympathetic nerves. The supine position is dangerous in pregnant women at term because of aortocaval compression by the gravid uterus. Therefore, during treatment of systemic toxicity, maternal hypotension, or fetal bradycardia following regional or neuraxial block, the parturient should be maintained in the left lateral decubitus position if possible, or manual displacement of the uterus off the great vessels be accomplished. Elevating the patient's legs and right-side-up positioning will help prevent decreases in blood pressure. The fetal heart rate also should be monitored continuously and electronic fetal monitoring is highly advisable.

Labor or Delivery

Spinal anesthesia is commonly used during labor and delivery. Bupivacaine hydrochloride, when administered properly, via the epidural route in doses 10 to 12 times the amount used in spinal anesthesia has been used for obstetrical analgesia and anesthesia without evidence of adverse effects on the fetus.

Spinal anesthesia may alter the forces of parturition through changes in uterine contractility or maternal expulsive efforts. Spinal anesthesia has also been reported to prolong the second stage of labor by removing the parturient's reflex urge to bear down or by interfering with motor function. The use of obstetrical anesthesia may increase the need for forceps assistance.

The use of some local anesthetic drug products during labor and delivery may be followed by diminished muscle strength and tone for the first day or two of life. This has not been reported with bupivacaine.

It is extremely important to avoid aortocaval compression by the gravid uterus during administrations of regional or neuraxial block to parturients. To do this, the patient must be maintained in the left lateral decubitus position or a blanket roll or sandbag may be placed beneath the right hip and the gravid uterus displaced to the left.

Data

Animal Data

Bupivacaine hydrochloride produced developmental toxicity when administered subcutaneously to pregnant rats and rabbits at doses 30-times the MHRD.

Bupivacaine hydrochloride was administered subcutaneously to rats at doses of 4.4, 13.3, and 40 mg/kg and to rabbits at doses of 1.3, 5.8, and 22.2 mg/kg during the period of organogenesis (implantation to closure of the hard palate). The high doses are approximately 30-times the daily MRHD of 12 mg/day on a mg dose/m^2 BSA basis. No embryo-fetal effects were observed in rats at the high dose which caused increased maternal lethality. An increase in embryo-fetal deaths was observed in rabbits at the high dose in the absence of maternal toxicity with the fetal No Observed Adverse Effect Level being approximately 8-times the MRHD on a BSA basis.

In a rat pre- and post-natal development study (dosing from implantation through weaning) conducted at subcutaneous doses of 4.4, 13.3, and 40 mg/kg, decreased pup survival was observed at the high dose. The high dose is approximately 30-times the daily MRHD of 12 mg/day on a BSA basis.

8.2 Lactation

Risk Summary

Lactation studies have not been conducted with bupivacaine. Bupivacaine has been reported to be excreted in human milk suggesting that the nursing infant could be theoretically exposed to a dose of the drug. MARCAINE SPINAL should be administered to lactating women only if clearly indicated. Studies assessing the effects of MARCAINE SPINAL in breastfed children have not been performed. Studies to assess the effect of MARCAINE SPINAL on milk production or excretion have not been performed. The developmental and health benefits of breastfeeding should be considered along with the mother's clinical need for bupivacaine and any potential adverse effects on the breastfed child from bupivacaine or from the underlying maternal condition.

8.4 Pediatric Use

MARCAINE SPINAL is approved for use in adults only. Administration of MARCAINE SPINAL in patients younger than 18 is not recommended.

8.5 Geriatric Use

Patients 65 years and over, particularly those with hypertension, may be at increased risk for developing hypotension while undergoing spinal anesthesia with MARCAINE SPINAL.

In clinical studies of bupivacaine, elderly patients exhibited a greater spread and higher maximal level of anesthesia than younger patients. Elderly patients also reached the maximal level of anesthesia more rapidly than younger patients, and exhibited a faster onset of motor blockade.

Differences in various pharmacokinetic parameters have been observed between elderly and younger patients [see Clinical Pharmacology (12.3)].

This product is known to be substantially excreted by the kidney, and the risk of adverse reactions to this drug may be greater in patients with impaired renal function. Because elderly patients are more likely to have decreased renal function, care should be taken in dose selection, and it may be useful to monitor renal function. Elderly patients may require lower doses of MARCAINE SPINAL.

8.6 Hepatic Impairment

Amide-type local anesthetics, such as bupivacaine, are metabolized by the liver. Patients with severe hepatic impairment, because of their inability to metabolize local anesthetics normally, are at a greater risk of developing toxic plasma concentrations, and potentially local anesthetic systemic toxicity. Therefore, consider reduced dosing and increased monitoring for local anesthetic systemic toxicity in patients with moderate to severe hepatic impairment treated with MARCAINE SPINAL [see Warnings and Precautions (5.10)].

8.7 Renal Impairment

Bupivacaine is known to be substantially excreted by the kidney, and the risk of adverse reactions to this drug may be greater in patients with renal impairment. This should be considered when selecting the MARCAINE SPINAL dosage [see Use in Specific Populations (8.5)].

10 OVERDOSAGE

Clinical Presentation

Acute emergencies from MARCAINE SPINAL are generally related to hypoventilation (and perhaps apnea) secondary to upward extension of spinal anesthesia or high plasma levels encountered during therapeutic use [see Warnings and Precautions (5.3), Adverse Reactions (6)]. Hypotension is commonly encountered during the conduct of spinal anesthesia due to loss of sympathetic tone, and sometimes, contributory mechanical obstruction of venous return due to the gravid uterus exerting pressure on the great vessels [see Warnings and Precautions (5.2), Adverse Reactions (6)].

If not treated immediately, convulsions with simultaneous hypoxia, hypercarbia, and acidosis plus myocardial depression from the direct effects of the local anesthetic may result in cardiac arrhythmias, bradycardia, asystole, ventricular fibrillation, or cardiac arrest. Respiratory abnormalities, including apnea, may occur. Hypoventilation or apnea due to a high or total spinal may produce these same signs and also lead to cardiac arrest if ventilatory support is not instituted. If cardiac arrest should occur, successful outcome may require prolonged resuscitative efforts.

Management

The first step in the management of systemic toxic reactions, as well as hypoventilation or apnea due to a high or total spinal, consists of immediate attention to the establishment and maintenance of a patent airway and effective assisted or controlled ventilation with 100% oxygen with a delivery system capable of permitting immediate positive airway pressure by mask. Endotracheal intubation, using drugs and techniques familiar to the clinician, may be indicated after initial administration of oxygen by mask if difficulty is encountered in the maintenance of a patent airway, or if prolonged ventilatory support (assisted or controlled) is indicated.

If necessary, use drugs to manage the convulsions. A bolus intravenous dose of benzodiazepine will counteract the CNS stimulation related to MARCAINE SPINAL. Immediately after the institution of ventilatory measures, evaluate the adequacy of the circulation. Supportive treatment of circulatory depression may require Advanced Cardiac Life Support measures.

Hypotension due to sympathetic relaxation may be managed by giving intravenous fluids (such as isotonic saline or lactated Ringer's solution), in an attempt to relieve mechanical obstruction of venous return, or by using vasopressor agents (such as ephedrine which increases myocardial contractility) and, if indicated, by giving plasma expanders or blood products.

11 DESCRIPTION

MARCAINE SPINAL (bupivacaine hydrochloride in dextrose injection) is an amide-local anesthetic and sterile hyperbaric aqueous solution. The route of administration for MARCAINE SPINAL is by subarachnoid injection. MARCAINE SPINAL contains bupivacaine hydrochloride, as the active pharmaceutical ingredient and also contains Dextrose, as baricity agent.

Bupivacaine Hydrochloride (monohydrate) chemical name is 2-piperidinecarboxamide, 1-butyl-N-(2,6-dimethylphenyl)-, monohydrochloride, monohydrate, a white crystalline powder that is freely soluble in 95 percent ethanol, soluble in water, and slightly soluble in chloroform or acetone. Bupivacaine Hydrochloride (monohydrate) has a molecular formula of C18H28N2O∙HCl∙H2O and molecular weight of 342.90 g/mol and has the following structural formula:

Dextrose chemical name is D-glucopyranose. Dextrose (anhydrous) has a molecular formula of C6H12O6, molecular weight of 180.16 g/mol and has the following structural formula:

MARCAINE SPINAL (bupivacaine hydrochloride in dextrose injection) is a clear and colorless sterile hyperbaric solution.

Each mL of MARCAINE SPINAL contains 7.5 mg bupivacaine hydrochloride (anhydrous) (equivalent to 7.9 mg of bupivacaine hydrochloride monohydrate), 82.5 mg dextrose (anhydrous) as baricity agent, and sodium hydroxide and hydrochloric acid as pH adjusters in water for injection.

MARCAINE SPINAL pH is between 4.0 and 6.5.

The specific gravity of MARCAINE SPINAL is between 1.030 and 1.035 at 25°C and 1.03 at 37°C.

MARCAINE SPINAL does not contain any preservatives.

12 CLINICAL PHARMACOLOGY

12.1 Mechanism of Action

Bupivacaine blocks the generation and the conduction of nerve impulses, presumably by increasing the threshold for electrical excitation in the nerve, by slowing the propagation of the nerve impulse, and by reducing the rate of rise of the action potential. In general, the progression of anesthesia is related to the diameter, myelination, and conduction velocity of affected nerve fibers. Clinically, the order of loss of nerve function is as follows: (1) pain, (2) temperature, (3) touch, (4) proprioception, and (5) skeletal muscle tone.

12.2 Pharmacodynamics

Systemic absorption of bupivacaine produces effects on the cardiovascular system and CNS. At blood concentrations achieved with normal therapeutic doses, changes in cardiac conduction, excitability, refractoriness, contractility, and peripheral vascular resistance are minimal. However, toxic blood concentrations depress cardiac conduction and excitability, which may lead to atrioventricular block, ventricular arrhythmias, and cardiac arrest, sometimes resulting in fatalities. In addition, myocardial contractility is depressed and peripheral vasodilation occurs, leading to decreased cardiac output and arterial blood pressure. These cardiovascular changes are more likely to occur after unintended intravascular injection of bupivacaine [see Warnings and Precautions (5.4)].

Following systemic absorption, bupivacaine can produce CNS stimulation, CNS depression, or both. Apparent central stimulation is manifested as restlessness, tremors and shivering, progressing to convulsions, followed by CNS depression and coma progressing ultimately to respiratory arrest. However, bupivacaine has a primary depressant effect on the medulla and on higher centers. The depressed stage may occur without a prior excited stage.

The duration of local anesthesia after administration of MARCAINE SPINAL is longer than that observed after administration of other commonly used short-acting local anesthetic. There appears to be a period of analgesia that persists after the resolution of the block and the return of sensation.

The onset of sensory blockade following spinal block with MARCAINE SPINAL is rapid (generally within one minute); maximum motor blockade and maximum dermatome level are achieved within 15 minutes in most cases. Duration of sensory blockade (time to return of complete sensation in the operative site or regression of two dermatomes) following MARCAINE SPINAL 12 mg averages 2 hours with or without 0.2 mg epinephrine. The time to return of complete motor ability with MARCAINE SPINAL 12 mg averages 3.5 hours without the addition of epinephrine and 4.5 hours if 0.2 mg epinephrine is added. When compared to equal milligram doses of hyperbaric tetracaine, the duration of sensory blockade was the same, but the time to complete motor recovery was longer for tetracaine. Addition of 0.2 mg epinephrine prolongs the motor blockade and time to first postoperative opioid with MARCAINE SPINAL.

12.3 Pharmacokinetics

Systemic plasma levels of bupivacaine following administration of MARCAINE SPINAL do not correlate with local efficacy.

Absorption

The rate of systemic absorption of bupivacaine is dependent upon the total dose and concentration of drug administered, the route of administration, the vascularity of the administration site, and the presence or absence of epinephrine in the anesthetic solution. A dilute concentration of epinephrine (1:200,000) usually reduces the rate of absorption and peak plasma concentration of bupivacaine, permitting the use of moderately larger total doses and sometimes prolonging the duration of action.

Distribution

Bupivacaine appears to cross the placenta by passive diffusion. The rate and degree of diffusion is governed by (1) the degree of plasma protein binding, (2) the degree of ionization, and (3) the degree of lipid solubility. Fetal/maternal ratios of bupivacaine appear to be inversely related to the degree of plasma protein binding, because only the free, unbound drug is available for placental transfer. Bupivacaine with a high protein binding capacity (95%) has a low fetal/maternal ratio (0.2 to 0.4). The extent of placental transfer is also determined by the degree of ionization and lipid solubility of the drug. Lipid soluble, nonionized drugs readily enter the fetal blood from the maternal circulation.

Depending upon the route of administration, bupivacaine is distributed to some extent to all body tissues, with high concentrations found in highly perfused organs such as the liver, lungs, heart, and brain.

Pharmacokinetic studies on the plasma profiles of bupivacaine after direct intravenous injection (MARCAINE SPINAL is not approved for intravenous use, and contraindicated for intravenous regional block, i.e. Bier Block) suggest a three-compartment open model. The first compartment is represented by the rapid intravascular distribution of the drug. The second compartment represents the equilibration of the drug throughout the highly perfused organs such as the brain, myocardium, lungs, kidneys, and liver. The third compartment represents an equilibration of the drug with poorly perfused tissues, such as muscle and fat.

Elimination

The half-life of bupivacaine in adults is 2.7 hours.

Metabolism

Amide-type local anesthetics such as bupivacaine are metabolized primarily in the liver via conjugation with glucuronic acid. Pipecoloxylidine is the major metabolite of bupivacaine. The elimination of drug from tissue distribution depends largely upon the ability of binding sites in the circulation to carry it to the liver where it is metabolized.

Excretion

The kidney is the main excretory organ for most local anesthetics and their metabolites. Urinary excretion is affected by urinary perfusion and factors affecting urinary pH. Only 6% of bupivacaine is excreted unchanged in the urine.

Specific Populations

Geriatric Patients

The total plasma clearance was decreased and the terminal half-life was lengthened in these patients.

Patients with Hepatic Impairment

Various pharmacokinetic parameters of the local anesthetics can be significantly altered by the presence of hepatic disease. Patients with hepatic disease, especially those with severe hepatic disease, may be more susceptible to the potential toxicities of the amide-type local anesthetics [see Use in Specific Populations (8.6)].

Patients with Renal Impairment

Various pharmacokinetic parameters of the local anesthetics can be significantly altered by the presence of renal disease, factors affecting urinary pH, and renal blood flow [see Use in Specific Populations (8.5, 8.7)].

13 NONCLINICAL TOXICOLOGY

13.1 Carcinogenesis, Mutagenesis, Impairment of Fertility

Carcinogenesis

Long-term studies in animals to evaluate the carcinogenic potential of bupivacaine hydrochloride have not been conducted.

Mutagenesis

The mutagenic potential of bupivacaine hydrochloride has not been determined.

Impairment of Fertility

The effect of bupivacaine on fertility has not been determined.

16 HOW SUPPLIED/STORAGE AND HANDLING

STORAGE AND HANDLING

Store at 20°C to 25°C (68°F to 77°F); excursions permitted between 15°C to 30°C (59°F to 86°F). [See USP Controlled Room Temperature.]

MARCAINE SPINAL solution may be autoclaved once at 15 pound pressure, 121°C (250°F) for 15 minutes. This product is clear and colorless. Do not use the solution if it is discolored or contains particulate matter.

Single-dose ampules of 2 mL MARCAINE SPINAL (bupivacaine hydrochloride in dextrose injection) (15 mg bupivacaine hydrochloride with 165 mg dextrose) are supplied as follows:

Unit of Sale | Concentration
NDC 0409-1761-02 Carton of 10 Uni-Amp™ single-dose ampules | 15 mg/2 mL (7.5 mg/mL)
NDC 0409-1761-10 Carton of 2 clamcells each containing 5 single-dose ampules | 15 mg/2 mL (7.5 mg/mL)
NDC 0409-1761-62 Case of 800 single-dose ampules | 15 mg/2 mL (7.5 mg/mL)

Discard the unused portion.

17 PATIENT COUNSELING INFORMATION

Allergic-Type Reactions

Assess if the patient has had allergic-type reactions to amide-type local anesthetics or to other formulation ingredients [see Contraindications (4), Adverse Reactions (6)].

Temporary Loss of Sensation and Motor Activity After Spinal Anesthesia

When appropriate, patients should be informed in advance that they may experience temporary loss of sensation and motor activity, usually in the lower half of the body, including the inability to move the legs, following proper administration of spinal anesthesia.

Methemoglobinemia

Inform patients that use of local anesthetics may cause methemoglobinemia, a serious condition that must be treated promptly. Advise patients or caregivers to seek immediate medical attention if they or someone in their care experience the following signs or symptoms: pale, gray, or blue colored skin (cyanosis), headache, rapid heart rate, shortness of breath, lightheadedness, or fatigue [see Warnings and Precautions (5.5)].

This product's labeling may have been updated. For the most recent prescribing information, please visit www.pfizer.com.

Distributed by Hospira, Inc., Lake Forest, IL 60045 USA

LAB-1179-4.0

PRINCIPAL DISPLAY PANEL - 2 mL Ampule Label -1761-19

#####AA
DMMMYYYY

LOT/EXP
PAA118784

2 mL
Rx only
NDC 0409-1761-19

Marcaine™ Spinal

bupivacaine hydrochloride
in dextrose injection, USP

Contains 7.5 mg bupivacaine HCl (anhydrous) and
82.5 mg dextrose (anhydrous) per mL. pH adjusted
between 4.0 and 6.5 with NaOH or HCl.

Distributed by Hospira, Inc.
Lake Forest, IL 60045 USA

Hospira

PRINCIPAL DISPLAY PANEL - 2 mL Ampule Unit Dose Pak Label

2 mL
UNI-AMP™ unit dose pak
Rx only
NDC 0409-1761-19

Marcaine™ Spinal

bupivacaine HCl in dextrose inj., USP

Contains 7.5 mg bupivacaine HCl (anhydrous) and 82.5 mg
dextrose (anhydrous) per mL. pH adjusted between 4.0 and
6.5 with NaOH or HCl.

Distributed by Hospira, Inc.
Lake Forest, IL 60045 USA

PAA118783

#####AA
DMMMYYYY

PRINCIPAL DISPLAY PANEL - 2 mL Ampule Unit Dose Pak Carton

2 mL
10 Ampuls UNI-AMP™ unit dose pak
NDC 0409-1761-02
Contains 10 of NDC 0409-1761-19
Rx only

STERILE HYPERBARIC SOLUTION FOR SPINAL ANESTHESIA

Marcaine™ Spinal

bupivacaine hydrochloride in dextrose injection, USP

Each mL contains 7.5 mg bupivacaine hydrochloride (anhydrous) and 82.5 mg dextrose
(anhydrous). pH adjusted between 4.0 and 6.5 with NaOH or HCl.

Hospira

PRINCIPAL DISPLAY PANEL - 2 mL Ampule Label - 1761-18

2 mL
NDC 0409-1761-18
Rx only

Marcaine® Spinal

bupivacaine hydrochloride 0.75% 15 mg/2 mL
(7.5 mg/mL) in dextrose 8.25% injection, USP
Contains 7.5 mg bupivacaine HCl (anhydrous)
and 82.5 mg dextrose (anhydrous) per mL. pH
adjusted between 4.0 and 6.5 with NaOH or HCl.

Dist. by Hospira, Inc., Lake Forest, IL 60045 USA
AP/DRUGS/08/2013 M.L.No. 08/VP/AP/2013/F/R

PAA236110

PRINCIPAL DISPLAY PANEL - 2 mL Ampule Cello Pack

5 x 2 mL Ampules
NDC 0409-1761-05

Rx only

Marcaine® Spinal

bupivacaine hydrochloride
0.75% 15 mg/2 mL (7.5 mg/mL)
in dextrose 8.25% injection, USP

Sterile Hyperbaric Solution for Spinal
Anesthesia

Distributed by Hospira, Inc. Lake Forest, IL 60045 USA

M.L.No. 08/VP/AP/2013/F/R
AP/DRUGS/08/2013

Hospira

PAA223332

PRINCIPAL DISPLAY PANEL - 2 mL Ampule Carton

10 x 2 mL Single-dose ampules

NDC 0409-1761-10
Contains 2 of NDC 0409-1761-05
Rx only

STERILE HYPERBARIC SOLUTION FOR SPINAL ANESTHESIA

Marcaine® Spinal

bupivacaine hydrochloride 0.75% 15 mg/2 mL (7.5 mg/mL)
in dextrose 8.25% injection, USP

Hospira